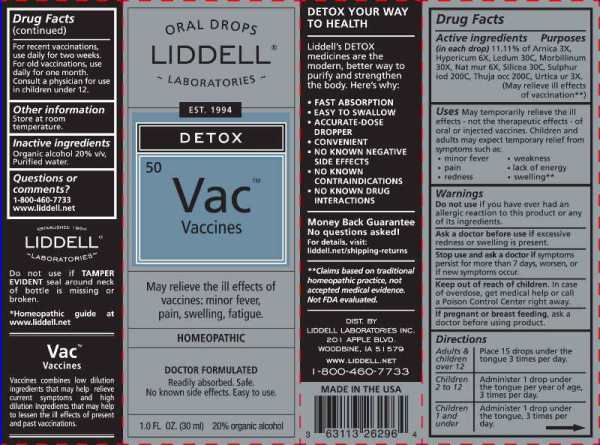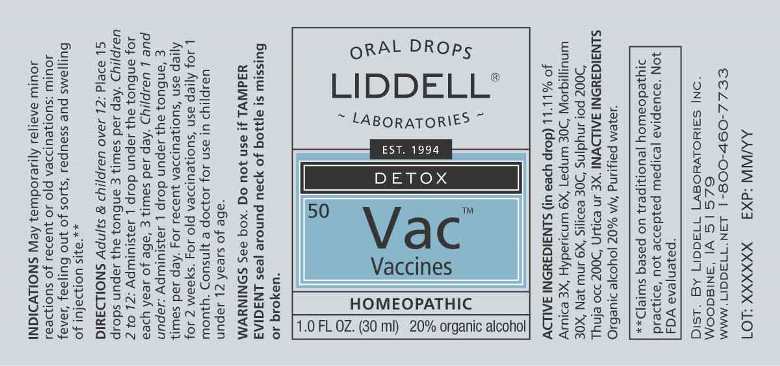 DRUG LABEL: Vaccines
NDC: 50845-0262 | Form: LIQUID
Manufacturer: Liddell Laboratories, Inc.
Category: homeopathic | Type: HUMAN OTC DRUG LABEL
Date: 20241104

ACTIVE INGREDIENTS: ARNICA MONTANA WHOLE 3 [hp_X]/1 mL; HYPERICUM PERFORATUM WHOLE 6 [hp_X]/1 mL; RHODODENDRON TOMENTOSUM LEAFY TWIG 30 [hp_C]/1 mL; MEASLES VIRUS 30 [hp_X]/1 mL; SODIUM CHLORIDE 6 [hp_X]/1 mL; SILICON DIOXIDE 30 [hp_C]/1 mL; SULFUR IODIDE 300 [hp_C]/1 mL; THUJA OCCIDENTALIS LEAFY TWIG 200 [hp_C]/1 mL; URTICA URENS WHOLE 3 [hp_X]/1 mL
INACTIVE INGREDIENTS: WATER; ALCOHOL

DRUG FACTS:

ACTIVE INGREDIENTS:

(in each drop) 11.11% of Arnica Montana 3X, Hypericum Perforatum 6X, Ledum Palustre 30C, Morbillinum 30X, Natrum Muriaticum 6X, Silicea 30C, Sulphur Iodatum 200C, Thuja Occidentalis 200C, Urtica

USES:

May temporarily relieve the ill effects - not the therapeutic effects - of oral or injected vaccines. Children and adults may expect temporary relief from symptoms such as:

• minor fever

• pain

• redness

• weakness

• lack of energy

• swelling**

**Claims based on traditional homeopathic practice, not accepted medical evidence. Not FDA evaluated.

WARNINGS:

Do not use if you have ever had an allergic reaction to this product or any of its ingredients.

Ask a doctor before use if excessive redness or swelling is present.

Stop use and ask a doctor if symptoms persist for more than 7 days, worsen, or if new symptoms occur.

Keep out of reach of children. In case of overdose, get medical help or call a Poison Control Center right away.

If pregnant or breast feeding, ask a doctor before using product.

Do not use if TAMPER EVIDENT seal around neck of bottle is missing or broken.

Other Information:

Store at room temperature.

Keep out of reach of children. In case of overdose, get medical help or call a Poison Control Center right away.

DIRECTIONS:

Adults & children over 12: Place 15 drops under the tongue 3 times per day.

Children 2 to 12: Administer 1 drop under the tongue per year of age, 3 times per day.

Children 1 and under: Administer 1 drop under the tongue, 3 times per day.

For recent vaccinations, use daily for two weeks. For old vaccinations, use daily for one month. Consult a physician for use in children under 12.

INDICATIONS:

May temporarily relieve the ill effects - not the therapeutic effects - of oral or injected vaccines. Children and adults may expect temporary relief from symptoms such as:

• minor fever

• pain

• redness

• weakness

• lack of energy

• swelling**

**Claims based on traditional homeopathic practice, not accepted medical evidence. Not FDA evaluated.

INACTIVE INGREDIENTS:

Organic alcohol 20% v/v, Purified water

QUESTIONS:

DIST. BY

LIDDELL LABORATORIES INC.

201 APPLE BLVD.

WOODBINE, IA 51579

WWW.LIDDELL.NET

1-800-460-7733

PACKAGE LABEL DISPLAY:

ORAL DROPS

LIDDELL

LABORATORIES

EST. 1994

DETOX

50 Vac

Vaccines

May relieve the ill effects of

vaccines: minor fever,

pain, swelling, fatigue.

HOMEOPATHIC

DOCTOR FORMULATED

Readily absorbed. Safe.

No known side effects. Easy to use.

1.0 FL. OZ. (30 ml)